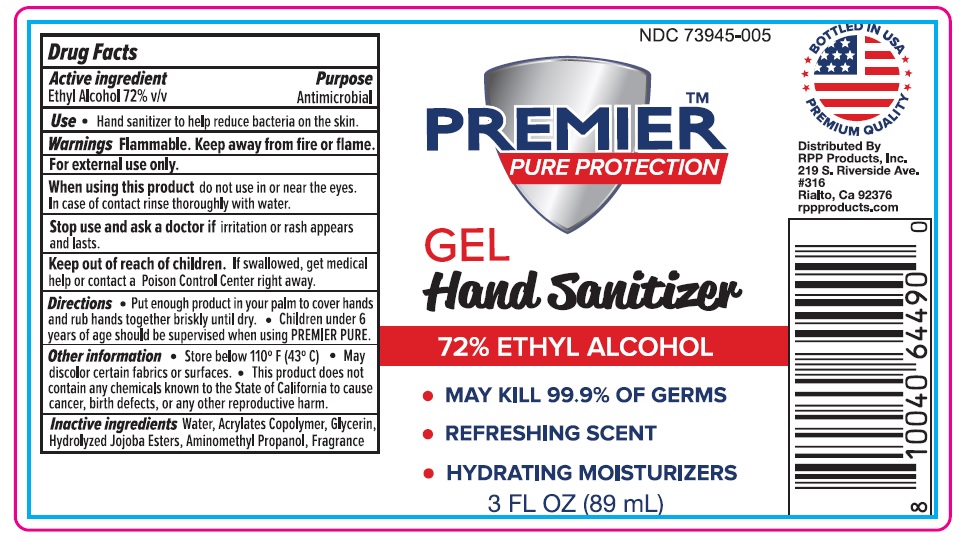 DRUG LABEL: Premier Pure Protection
NDC: 73945-005 | Form: GEL
Manufacturer: RPP Products, Inc.
Category: otc | Type: HUMAN OTC DRUG LABEL
Date: 20200620

ACTIVE INGREDIENTS: ALCOHOL 72 mL/100 mL
INACTIVE INGREDIENTS: WATER; ACRYLATES/VINYL ISODECANOATE CROSSPOLYMER (10000 MPA.S NEUTRALIZED AT 0.5%); GLYCERIN; HYDROLYZED JOJOBA ESTERS (POTASSIUM SALTS); AMINOMETHYLPROPANOL

Active Ingredient

Ethyl Alcohol 72% v/v.

Purpose

Antimicrobial

Use

Hand sanitizer to help reduce bacteria on the skin.

Warnings

Flammable. Keep away from fire or flame

For external use only.

When using this product do not use in or near the eyes.In case of contact rinse thoroughly with water.

Stop use and ask a doctor if irritation or rash appears and lasts.

Keep out of reach of children. If swallowed, get medical help or contact a Poison Control Center right away.

Directions

- Put enough product in your palm to cover hands and rub hands together briskly until dry.
- Children under 6 years of age should be supervised when using PREMIER PURE.

Other information

- Store below 110º F (43º C).
- May discolor certain fabrics or surfaces.
- This product does not contain any chemicals known to the State of California to cause cancer, birth defects, or any other reproductive harm.

Inactive ingredients

Water, Acrylates Copolymer, Glycerin, Hydrolyzed Jojoba Esters, Aminomethyl Propanol, Fragrance